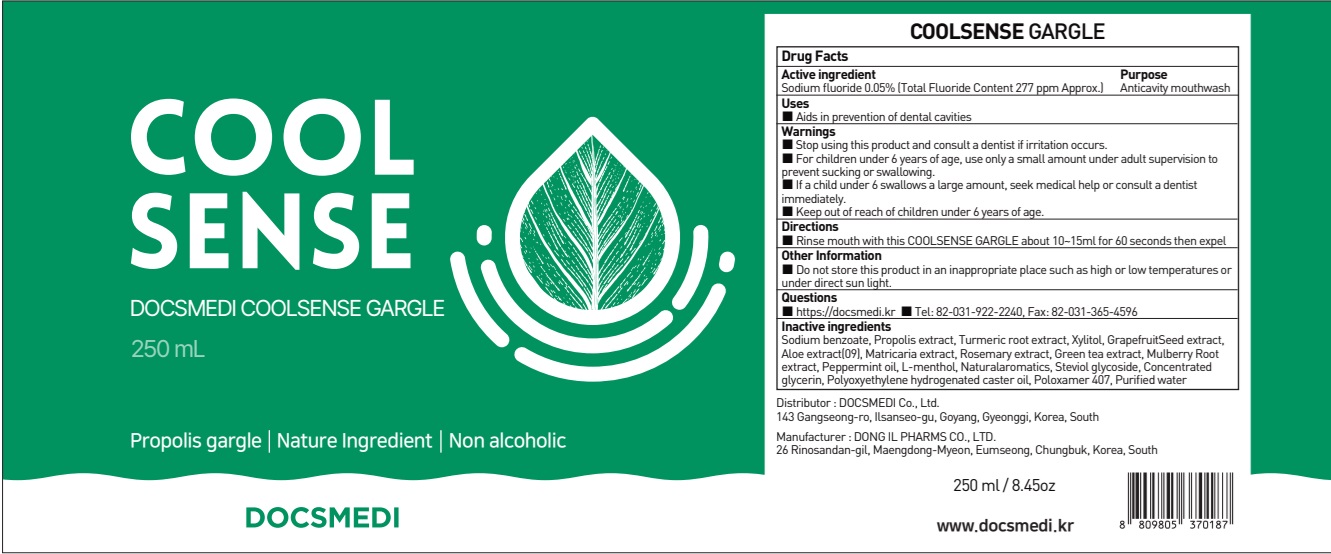 DRUG LABEL: Cool sense Care Plus
NDC: 73242-1121 | Form: MOUTHWASH
Manufacturer: DONG IL PHARMS CO., LTD.
Category: otc | Type: HUMAN OTC DRUG LABEL
Date: 20251125

ACTIVE INGREDIENTS: SODIUM FLUORIDE 0.05 g/100 mL
INACTIVE INGREDIENTS: SODIUM BENZOATE; PROPOLIS WAX

ACTIVE INGREDIENT

Sodium fluoride 0.05%
(Total Fluoride Content 277 ppm Approx.)

Inactive ingredients

Sodium benzoate, Propolis extract, Turmeric root extract, Xylitol, GrapefruitSeed extract, Aloe extract(09), Matricaria extract, rosemary extract, Green tea extract, Mulberry Root extract, Peppermint oil, L-menthol, Naturalaromatics, Steviol glycoside, Concentrated glycerin, Polyoxyethylene hydrogenated caster oil, Poloxamer 407, Purified water

PURPOSE

Anticavity mouthwash

WARNINGS

■ Stop using this product and consult a dentist if irritation occurs.

■ For children under 6 years of age, use only a small amount under adult supervision to prevent sucking or swallowing.

■ If a child under 6 swallows a large amount, seek medical help or consult a dentist immediately.

■ Keep out of reach of children under 6 years of age.

KEEP OUT OF REACH OF CHILDREN

■ Keep out of the reach of children under 6 years of age.

Uses

■ Aids in prevention of dental cavities

Directions

■ Rinse mouth with this COOLSENSE GARGLE about 10~15ml for 60 seconds then expel

Other Information

■ Do not store this product in an inappropriate place such as high or low temperatures or under direct sun light

Questions

■ https://docsmedi.kr

■ Tel: 82-031-922-2240, Fax: 82-031-365-4596